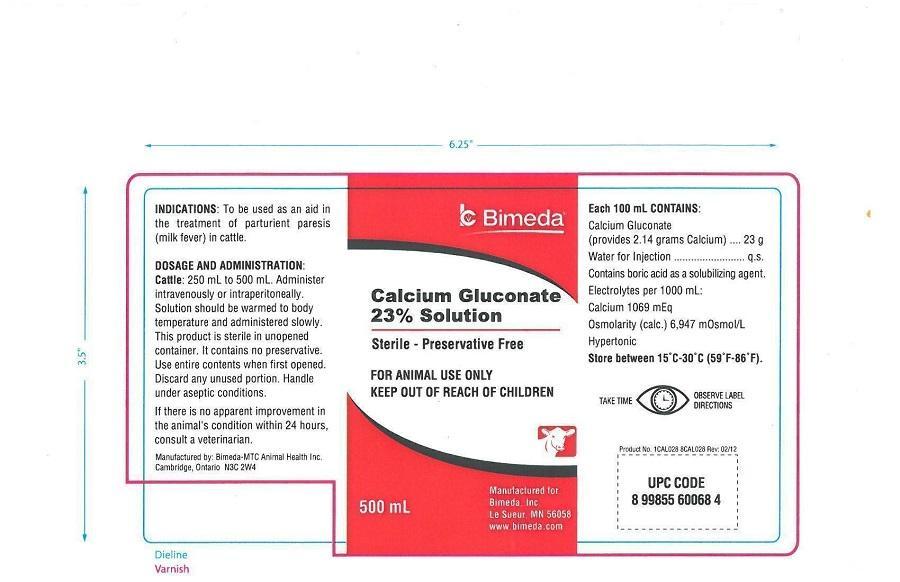 DRUG LABEL: Calcium Gluconate
NDC: 61133-0297 | Form: INJECTION
Manufacturer: Bimeda, Inc.
Category: animal | Type: OTC ANIMAL DRUG LABEL
Date: 20181128

ACTIVE INGREDIENTS: CALCIUM GLUCONATE 23 g/100 mL

INDICATIONS AND USAGE

INDICATIONS: To be used as an aid in the treatment of parturient paresis (milk fever) in cattle.

DOSAGE AND ADMINISTRATION:

Cattle: 250 mL to 500 mL. Administer intravenously or intraperitoneally. Solution should be warmed to body temperature and administered slowly. This product is sterile in unopened container. It contains no preservative. Use entire contents when first opened. Discard any unused portion. Handle under aseptic conditions.

If there is no apparent improvement in the animal's condition within 24 hours, consult a veterinarian.

EACH 100 mL CONTAINS:

Calcium Gluconate

(provides 2.14 grams Calcium)..........................23 grams

Water for Injection...................................................q.s.

Contains boric acid as a solubilizing agent.

ELECTROLYTES PER 1000 mL:

Calcium 1069 mEq

Osmolarity (calc.) 6,947 m0smol/L

Hypertonic

STORAGE: Store between 15⁰C - 30⁰C (59⁰F - 86⁰F).